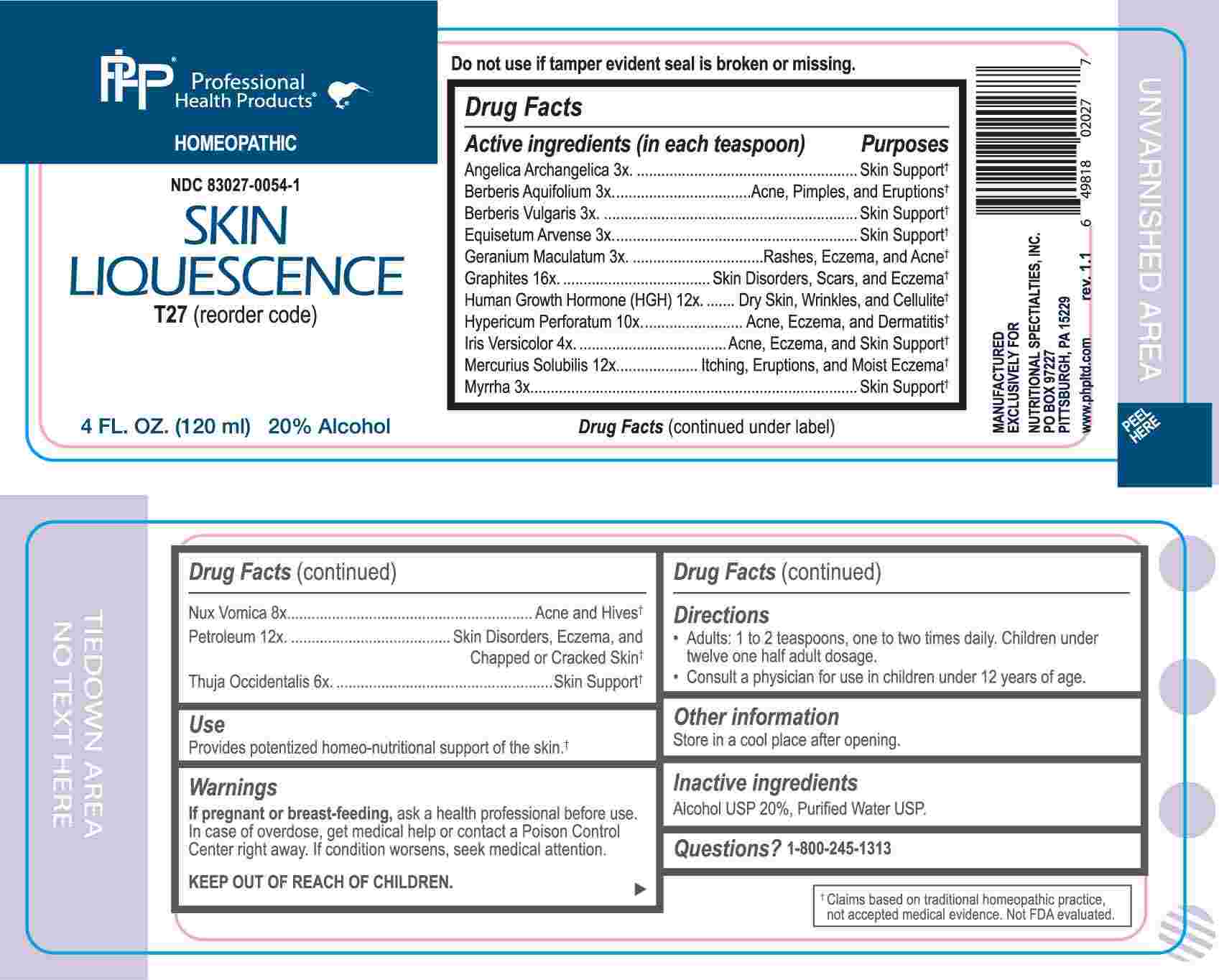 DRUG LABEL: Skin Liquescence
NDC: 83027-0054 | Form: LIQUID
Manufacturer: Nutritional Specialties, Inc.
Category: homeopathic | Type: HUMAN OTC DRUG LABEL
Date: 20250506

ACTIVE INGREDIENTS: ANGELICA ARCHANGELICA ROOT 3 [hp_X]/1 mL; BERBERIS AQUIFOLIUM ROOT BARK 3 [hp_X]/1 mL; BERBERIS VULGARIS ROOT BARK 3 [hp_X]/1 mL; EQUISETUM ARVENSE TOP 3 [hp_X]/1 mL; GERANIUM MACULATUM ROOT 3 [hp_X]/1 mL; MYRRH 3 [hp_X]/1 mL; IRIS VERSICOLOR ROOT 4 [hp_X]/1 mL; THUJA OCCIDENTALIS LEAFY TWIG 6 [hp_X]/1 mL; STRYCHNOS NUX-VOMICA SEED 8 [hp_X]/1 mL; HYPERICUM PERFORATUM WHOLE 10 [hp_X]/1 mL; SOMATROPIN 12 [hp_X]/1 mL; MERCURIUS SOLUBILIS 12 [hp_X]/1 mL; KEROSENE 12 [hp_X]/1 mL; GRAPHITE 16 [hp_X]/1 mL
INACTIVE INGREDIENTS: WATER; ALCOHOL

DRUG FACTS:

ACTIVE INGREDIENTS:

(in each teaspoon) Angelica Archangelica 3X, Berberis Aquifolium 3X, Berberis Vulgaris 3X, Equisetum Arvense 3X, Geranium Maculatum 3X, Graphites 16X, Human Growth Hormone (HGH) 12X, Hypericum Perforatum 10X, Iris Versicolor 4X, Mercurius Solubilis 12X, Myrrha 3X, Nux Vomica 8X, Petroleum 12X, Thuja Occidentalis 6X.

PURPOSE:

Angelica Archangelica – Skin Support,† Berberis Aquifolium – Acne, Pimples, and Eruptions, † Berberis Vulgaris – Skin Support, † Equisetum Arvense – Sin Support, † Geranium Maculatum – Rashes, Eczema, and Acne,† Graphites – Skin Disorders, Scars, and Eczema, † Human Growth Hormone (HGH) – Dry Skin, Wrinkles, and Cellulite, † Hypericum Perforatum – Acne, Eczema, and Dermatitis, † Iris Versicolor – Acne, Eczema, and Skin Support, † Mercurius Solubilis – Itching, Eruptions, and Moist Eczema, † Myrrha – Skin Support, † Nux Vomica – Acne and Hives, † Petroleum – Skin Disorders, Eczema, and Chapped or Cracked Skin, † Thuja Occidentalis – Skin Support †

†Claims based on traditional homeopathic practice, not accepted medical evidence. Not FDA evaluated.

USES:

Provides potentized homeo-nutritional support of the Skin.†

†Claims based on traditional homeopathic practice, not accepted medical evidence. Not FDA evaluated.

WARNINGS:

If pregnant or breast-feeding, ask a health professional before use.

In case of overdose, get medical help or contact a Poison Control Center right away.

If condition worsens, seek medical attention.

KEEP OUT OF REACH OF CHILDREN

Do not use if tamper evident seal is broken or missing.

Store in a cool place after opening

KEEP OUT OF REACH OF CHILDREN:

In case of overdose, get medical help or contact a Poison Control Center right away.

DIRECTIONS:

• Adults: 1 to 2 teaspoons, one to two times daily. Children under twelve one half adult dosage.

Consult a physician for use in children under 12 years of age.

INACTIVE INGREDIENTS:

Alcohol USP 20%, Purified Water USP.

QUESTIONS:

MANUFACTURED EXCLUSIVELY FOR

NUTRITIONAL SPECIALTIES, INC.

PO BOX 97227

PITTSBURG, PA 15229

www.phpltd.com

1-800-245-1313

PACKAGE LABEL DISPLAY:

Professional

Health Products

HOMEOPATHIC

NDC 83027-0054-1

SKIN LIQUESCENCE

4 FL. OZ (120 ml)